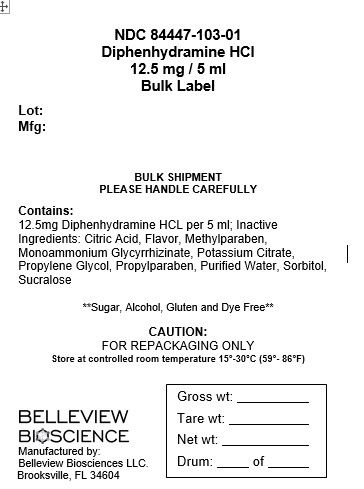 DRUG LABEL: Diphenhydramine HCL
NDC: 84447-103 | Form: SOLUTION
Manufacturer: Belleview Biosciences
Category: otc | Type: HUMAN OTC DRUG LABEL
Date: 20250612

ACTIVE INGREDIENTS: DIPHENHYDRAMINE HYDROCHLORIDE 12.5 mg/5 mL
INACTIVE INGREDIENTS: WATER; NONCRYSTALLIZING SORBITOL SOLUTION; PROPYLENE GLYCOL; SUCRALOSE; CITRIC ACID; POTASSIUM CITRATE; METHYLPARABEN; PROPYLPARABEN; AMMONIUM GLYCYRRHIZINATE TRIHYDRATE; CHERRY

Diphenhydramine HCL

DOSAGE AND ADMINISTRATION

Directions: Take every 4-6 hours, or as directed by doctor. * Do NOT exceed the recommended dose

Age | Dose
Adults and Children 12 years of age and over | take 10 to 20 mL (2 to 4 tsp), not to exceed 300 mg in 24 hours
Children 6 to under 12 years of age | take 5 to 10 mL (1 to 2 tsp) not to exceed 150 mg in 24 hours
Children under 6 years of age | Consult a doctor

Warnings:

Do not use: ■ with any other product containing

diphenhydramine, even one used on skin ■ to make a

child sleepy

Ask a doctor before use if you have: ■ a breathing

problem such as emphysema or chronic bronchitis

■ glaucoma ■ trouble urinating due to the enlarged

prostate gland

Ask a doctor or pharmacist before use if you are

taking sedatives or tranquilizers.

When using this product: ■ excitability might occur,

especially in children ■ marked drowsiness may occur

■ avoid alcoholic drinks ■ alcohol, sedatives, and

tranquilizers may increase drowsiness effect ■ be careful

when driving a motor vehicle or operating machinery

If pregnant or breast-feeding, ask a health

professional before use.

Keep out of reach of children.

In case of overdose, get medical help or contact a

Poison Control Center (1-800-222-1222) right away.

Inactive Ingredients: Citric Acid,

Flavor, Methylparaben, Monoammonium

Glycyrrhizinate, Potassium Citrate, Propylene Glycol,

Propylparaben, Purified Water, Sorbitol, Sucralose

INDICATIONS AND USAGE

Uses: Temporarily relieves these symptoms due

to hay fever or other upper respiratory allergies: ■

runny nose ■ sneezing ■ itchy, watery eyes ■

itching of the nose or throat ■ Temporarily relieves

these symptoms due to the common cold: ■ runny

nose ■ sneezing

Keep out of reach of children.

In case of overdose, get medical help or contact a

Poison Control Center (1-800-222-1222) right away.

Purpose: Antihistamine

Active Ingredient (in each 5 mL tsp)

Diphenhydramine HCL, 12.5 mg